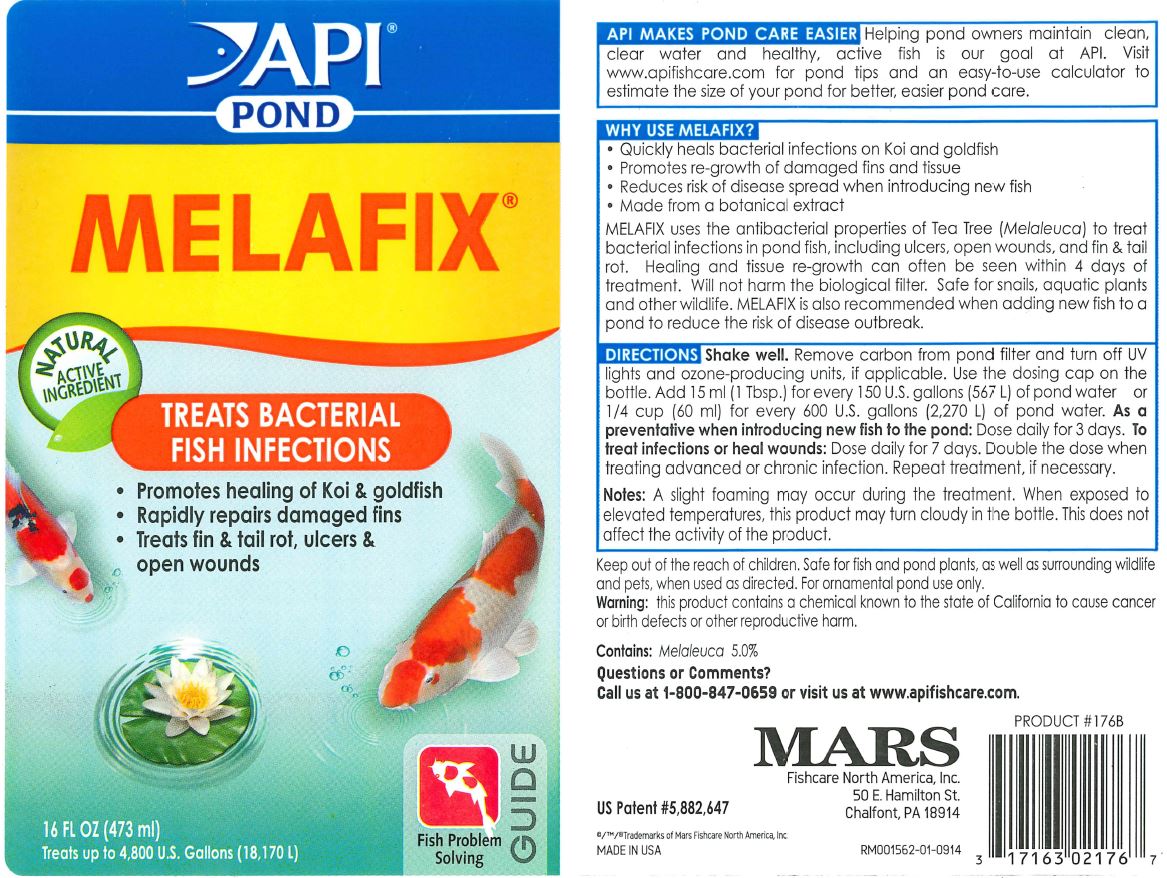 DRUG LABEL: API POND MELAFIX
NDC: 17163-176 | Form: LIQUID
Manufacturer: MARS FISHCARE NORTH AMERICA, INC.
Category: animal | Type: OTC ANIMAL DRUG LABEL
Date: 20191219

ACTIVE INGREDIENTS: CAJUPUT OIL 5 g/100 mL

Drug Label

DESCRIPTION

API MAKES POND CARE EASIER

Helping pond owners maintain clean, clear water and healthy, active fish is good at API. Visit www.apifishcare.com for pond tips and an easy-to-use calculator to estimate the size of your pond for better, easier pond care.

INDICATIONS AND USAGE

WHY USE MELAFIX?

Quickly heals bacterial infections on Koi and goldfish

Promotes re-growth of damaged fins and tissue

Reduces risk of disease spread when introducing new fish

Made from a botanical extract

MELAFIX uses the antibacterial properties of Tea Tree (Melaleuca) to treat bacterial infections in pond fish, including ulcers, open wounds, and fin and tail rot. Healing and tissue re-growth can often be seen within 4 days of treatment. Will not harm the biological filter. Safe for snails, aquatic plants and other wildlife. MELAFIX is also recommended when adding new fish to a pond to reduce the risk of disease outbreak.

DIRECTIONS

Shake well. Remove carbon from pond filter and turn off UV lights and ozone-producing units, if applicable. Use the dosing cap on the bottle. Add 15 ml (1 Tbsp.) for every 150 U.S. gallons (567 L) of pond water or 1/4 cup (60 ml) for every 600 U.S. gallons (2, 270 L) of pond water.

As a preventative when introducing new fish to the pond: Dose daily for 3 days.

To treat infections or heal wounds: Dose daily for 7 days. Double the dose when treating advanced or chronic infection. Repeat treatment, if necessary.

Notes: A slight foaming may occur during the treatment. When exposed to elevated temperatures, this product may turn cloudy in the bottle. This does not affect the activity of the product.

Keep out of reach of children.

Safe for fish and pond plants, as well as surrounding wildlife and pets, when used as directed. For ornamental pond use only

Warning: this product contains a chemical known to the state of California to cause cancer or birth defects or other reproductive harm.

ACTIVE INGREDIENT

Contains: Melaleuca 5.0%

Questions or Comments?

Call us at 1-800-847-0659 or visit us at www.apifishcare.com.

PACKAGE LABEL

API

POND

MELAFIX

NATURAL

ACTIVE

INGREDIENT

TREATS BACTERIAL

FISH INFECTIONS

Promotes healing of Koi and goldfish

Rapidly repairs damaged fins

Treats fin and tail rot, ulcers and open sores

16 FL OZ (473 ml)

Treats up to 4,800 U.S. Gallons (18,170 L)

Fish Problem

Solving

Guide

US Patent 5,882,647

MADE IN USA

PRODUCT 176B